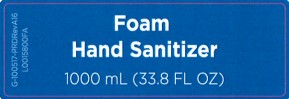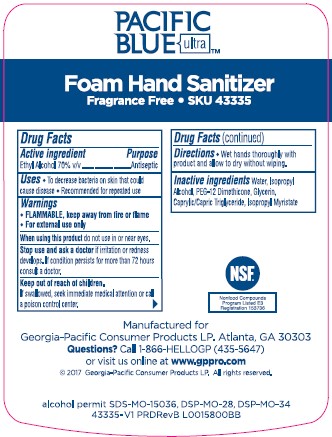 DRUG LABEL: Pacific Blue Ultra Foaming


NDC: 54622-701 | Form: SOLUTION
Manufacturer: Georgia-Pacific Consumer Products LP
Category: otc | Type: HUMAN OTC DRUG LABEL
Date: 20260204

ACTIVE INGREDIENTS: ALCOHOL 70 mg/1 mL
INACTIVE INGREDIENTS: ISOPROPYL MYRISTATE; WATER; ISOPROPYL ALCOHOL; PEG-12 DIMETHICONE; GLYCERIN; GLYCERYL CAPRYLATE/CAPRATE

Pacific Blue Ultra 701.000/701AA
70% Alcohol Hand Sanitizer

Claims

PACIFIC BLUE ultra

Foam Hand Sanitizer

Fragrance Free • SKU 43335

Active ingredient

Ethyl Alcohol 70% v/v

Purpose

Antiseptic

Uses

- To decrease bacteria on the skin that could cause disease
- Recommended for repeated use

Warnings

- FLAMMABLE, keep away from fire and flame
- For external use only

When using this product

do not use in or near eyes.

Stop use and ask a doctor

if irritation or redness develops. If condition persists for more than 72 hours consult a doctor.

Keep out of reach of children.

If swallowed, seek immediate medical attention or call a poison control center.

Directions

Wet hands thoroughly with product and allow to dry without wiping.

Inactive ingredients

Water, Isopropyl Alcohol, PEG-12 Dimethicone, Glycerin, Caprylic/Capric Triglyceride, Isopropyl Myristate

ADVERSE REACTION

Manufactured for Georgia-Pacific Consumer Products LP. Atlanta, GA 30303

Questions? Call 1-866-HELLOGP (435-5647) or visit us online at www.gppro.com

©2017 Georgia Pacific Consumer Products LP. All rights reserved.

alcohol permit SDS-MO-15036, DSP-MO-28, DSP-MO-34

43335-V1 PRDRevB

principal display panel

Foam Hand Sanitizer

1000 mL (33.8 FL OZ)

G-100517-PRDRevA16